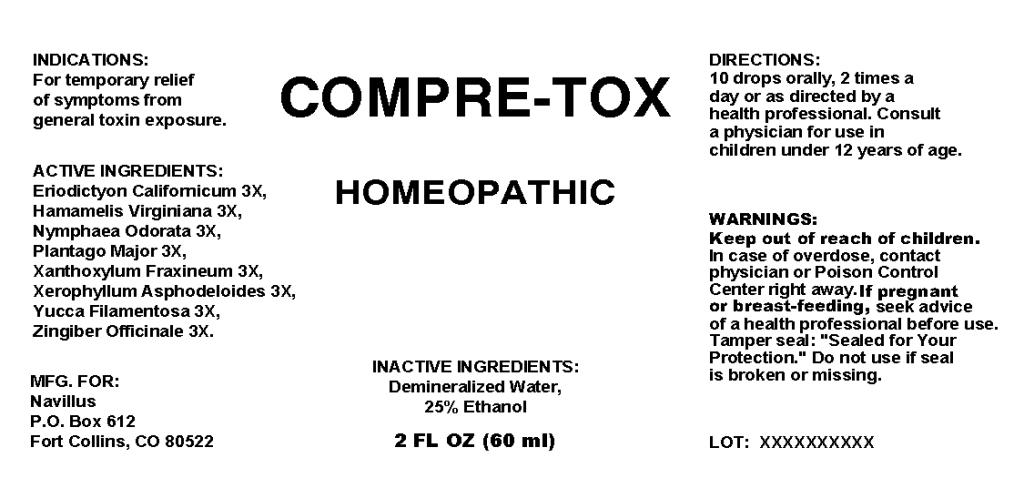 DRUG LABEL: Compre Tox
NDC: 57520-0556 | Form: LIQUID
Manufacturer: Apotheca Company
Category: homeopathic | Type: HUMAN OTC DRUG LABEL
Date: 20101025

ACTIVE INGREDIENTS: ERIODICTYON CALIFORNICUM LEAF 3 [hp_X]/1 mL; HAMAMELIS VIRGINIANA ROOT BARK/STEM BARK 3 [hp_X]/1 mL; NYMPHAEA ODORATA ROOT 3 [hp_X]/1 mL; PLANTAGO MAJOR 3 [hp_X]/1 mL; ZANTHOXYLUM AMERICANUM BARK 3 [hp_X]/1 mL; XEROPHYLLUM ASPHODELOIDES 3 [hp_X]/1 mL; YUCCA FILAMENTOSA 3 [hp_X]/1 mL; GINGER 3 [hp_X]/1 mL
INACTIVE INGREDIENTS: WATER; ALCOHOL

Compre Tox

ACTIVE INGREDIENT

ACTIVE INGREDIENTS: Eriodictyon californicum 3X, Hamamelis Virginiana 3X, Nymphaea odorata 3X, Plantago major 3X, Xanthoxylum fraxineum 3X, Xerophyllum asphodeloides 3X, Yucca filamentosa 3X, Zingiber officinale 3X.

PURPOSE

INDICATIONS: For temporary relief of symptoms from general toxin exposure.

WARNINGS

WARNINGS: Keep out of reach of children. In case of overdose, contact physician or Poison Control Center right away.

If pregnant or breast-feeding, seek advice of a health professional before use.

Tamper seal: "Sealed for Your Protection." Do not use if seal is broken or missing.

DOSAGE AND ADMINISTRATION

DIRECTIONS: 10 drops orally, 2 times a day or as directed by a health professional. Consult a physician for use in children under 12 years of age.

INACTIVE INGREDIENTS: Demineralized water, 25% Ethanol.

KEEP OUT OF REACH OF CHILDREN. In case of overdose, contact physician or Poison Control Center right away.

INDICATIONS AND USAGE

INDICATIONS: For temporary relief of symptoms from general toxin exposure.

QUESTIONS

MFG. FOR:

Navillus

P.O. Box 612

Fort Collins, CO 80522

PACKAGE LABEL

COMPRE-TOX

HOMEOPATHIC

1 FL OZ (60 ml)